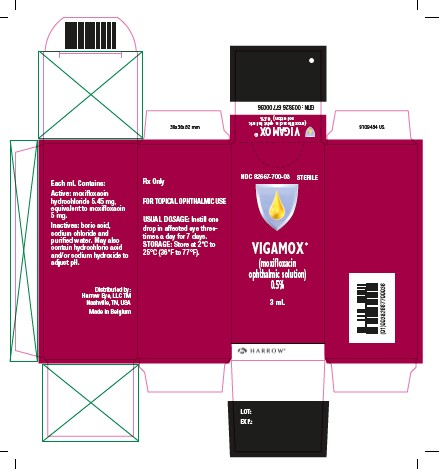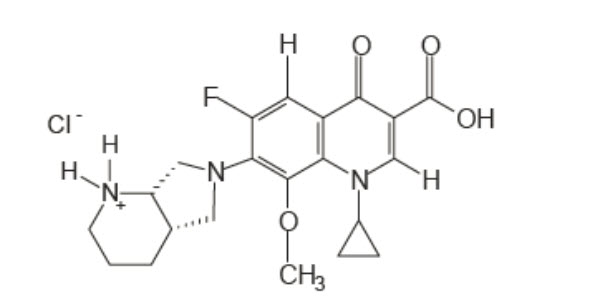 DRUG LABEL: VIGAMOX
NDC: 82667-700 | Form: SOLUTION/ DROPS
Manufacturer: Harrow Eye, LLC
Category: prescription | Type: HUMAN PRESCRIPTION DRUG LABEL
Date: 20260122

ACTIVE INGREDIENTS: MOXIFLOXACIN HYDROCHLORIDE 5 mg/1 mL
INACTIVE INGREDIENTS: HYDROCHLORIC ACID; SODIUM HYDROXIDE; BORIC ACID; SODIUM CHLORIDE; WATER

HIGHLIGHTS OF PRESCRIBING INFORMATION

These highlights do not include all the information needed to use VIGAMOX safely and effectively. See full prescribing information for VIGAMOX.
VIGAMOX®(moxifloxacin ophthalmic solution), for topical ophthalmic use
Initial U.S. Approval: 1999

1 INDICATIONS AND USAGE

VIGAMOX is a topical fluoroquinolone anti-infective indicated for the treatment of bacterial conjunctivitis caused by susceptible strains of the following organisms:

Corynebacteriumspecies* , Micrococcus luteus*, Staphylococcus aureus, Staphylococcus epidermidis, Staphylococcus haemolyticus, Staphylococcus hominis, Staphylococcus warneri*, Streptococcus pneumoniae, Streptococcus viridansgroup , Acinetobacter lwoffii*, Haemophilus influenzae, Haemophilus parainfluenzae*, Chlamydia trachomatis

*Efficacy for this organism was studied in fewer than 10 infections. (1)

2 DOSAGE AND ADMINISTRATION

Instill one drop in the affected eye 3 times a day for 7 days. (2)

3 DOSAGE FORMS AND STRENGTHS

Ophthalmic solution containing moxifloxacin 0.5%. (3)

4 CONTRAINDICATIONS

VIGAMOX is contraindicated in patients with a history of hypersensitivity to moxifloxacin, to other quinolones, or to any of the components in this medication. (4)

5 WARNINGS AND PRECAUTIONS

- Hypersensitivity Reactions: Hypersensitivity and anaphylaxis have been reported with systemic use of moxifloxacin. (5.1)
- Prolonged Use: May result in overgrowth of non-susceptible organisms, including fungi. If superinfection occurs, discontinue use and institute alternative therapy. (5.2)
- Avoid Contact Lens Wear: Patients should not wear contact lenses if they have signs or symptoms of bacterial conjunctivitis. (5.3)

6 ADVERSE REACTIONS

The most frequently reported ocular adverse events were conjunctivitis, decreased visual acuity, dry eye, keratitis, ocular discomfort, ocular hyperemia, ocular pain, ocular pruritus, subconjunctival hemorrhage, and tearing. These events occurred in approximately 1% to 6% of patients. (6)

To report SUSPECTED ADVERSE REACTIONS, contact Harrow Eye, LLC at 844-446-6979 or FDA at 1-800-FDA-1088 or www.fda.gov/medwatch.

FULL PRESCRIBING INFORMATION

1 INDICATIONS AND USAGE

VIGAMOX®is indicated for the treatment of bacterial conjunctivitis caused by susceptible strains of the following organisms:

Corynebacteriumspecies*
Micrococcus luteus*
Staphylococcus aureus
Staphylococcus epidermidis
Staphylococcus haemolyticus
Staphylococcus hominis
Staphylococcus warneri*
Streptococcus pneumoniae
Streptococcus viridansgroup
Acinetobacter lwoffii*
Haemophilus influenza
Haemophilus parainfluenzae*
Chlamydia trachomatis

*Efficacy for this organism was studied in fewer than 10 infections.

2 DOSAGE AND ADMINISTRATION

Instill one drop in the affected eye 3 times a day for 7 days. VIGAMOX is for topical ophthalmic use.

3 DOSAGE FORMS AND STRENGTHS

Ophthalmic solution containing moxifloxacin 0.5%.

4 CONTRAINDICATIONS

VIGAMOX is contraindicated in patients with a history of hypersensitivity to moxifloxacin, to other quinolones, or to any of the components in this medication.

5 WARNINGS AND PRECAUTIONS

5.1 Hypersensitivity Reactions

In patients receiving systemically administered quinolones, including moxifloxacin, serious and occasionally fatal hypersensitivity (anaphylactic) reactions have been reported, some following the first dose. Some reactions were accompanied by cardiovascular collapse, loss of consciousness, angioedema (including laryngeal, pharyngeal or facial edema), airway obstruction, dyspnea, urticaria, and itching. If an allergic reaction to moxifloxacin occurs, discontinue use of the drug. Serious acute hypersensitivity reactions may require immediate emergency treatment. Oxygen and airway management should be administered as clinically indicated.

5.2 Growth of Resistant Organisms With Prolonged Use

As with other anti-infectives, prolonged use may result in overgrowth of non-susceptible organisms, including fungi. If superinfection occurs, discontinue use and institute alternative therapy. Whenever clinical judgment dictates, the patient should be examined with the aid of magnification, such as slit-lamp biomicroscopy, and, where appropriate, fluorescein staining.

5.3 Avoidance of Contact Lens Wear

Patients should be advised not to wear contact lenses if they have signs or symptoms of bacterial conjunctivitis.

6 ADVERSE REACTIONS

Because clinical trials are conducted under widely varying conditions, adverse reaction rates observed in the clinical trials of a drug cannot be directly compared to the rates in the clinical trials of another drug and may not reflect the rates observed in practice.

The most frequently reported ocular adverse events were conjunctivitis, decreased visual acuity, dry eye, keratitis, ocular discomfort, ocular hyperemia, ocular pain, ocular pruritus, subconjunctival hemorrhage, and tearing. These events occurred in approximately 1%-6% of patients.

Nonocular adverse events reported at a rate of 1%-4% were fever, increased cough, infection, otitis media, pharyngitis, rash, and rhinitis.

7 DRUG INTERACTIONS

Drug-drug interaction studies have not been conducted with VIGAMOX®. In vitrostudies indicate that moxifloxacin does not inhibit CYP3A4, CYP2D6, CYP2C9, CYP2C19, or CYP1A2, indicating that moxifloxacin is unlikely to alter the pharmacokinetics of drugs metabolized by these cytochrome P450 isozymes.

8 USE IN SPECIFIC POPULATIONS

8.1 Pregnancy

Risk Summary

There are no adequate and well-controlled studies with VIGAMOX®in pregnant women to inform any drug-associated risks.

Oral administration of moxifloxacin to pregnant rats and monkeys and intravenously to pregnant rabbits during the period of organogenesis did not produce adverse maternal or fetal effects at clinically relevant doses. Oral administration of moxifloxacin to pregnant rats during late gestation through lactation did not produce adverse maternal, fetal or neonatal effects at clinically relevant doses (see Data).

Data

Animal Data

Embryo-fetal studies were conducted in pregnant rats administered with 20, 100, or 500 mg/kg/day moxifloxacin by oral gavage on Gestation Days 6 to 17, to target the period of organogenesis. Decreased fetal body weight and delayed skeletal development were observed at 500 mg/kg/day [277 times the human area under the curve (AUC) at the recommended human ophthalmic dose]. The No-Observed-Adverse-Effect-Level (NOAEL) for developmental toxicity was 100 mg/kg/day (30 times the human AUC at the recommended human ophthalmic dose).

Embryo-fetal studies were conducted in pregnant rabbits administered with 2, 6.5, or 20 mg/kg/day moxifloxacin by intravenous administration on Gestation Days 6 to 20, to target the period of organogenesis. Abortions, increased incidence of fetal malformations, delayed fetal skeletal ossification, and reduced placental and fetal body weights were observed at 20 mg/kg/day (1086 times the human AUC at the recommended human ophthalmic dose), a dose that produced maternal body weight loss and death. The NOAEL for developmental toxicity was 6.5 mg/kg/day (246 times the human AUC at the recommended human ophthalmic dose).

Pregnant cynomolgus monkeys were administered moxifloxacin at doses of 10, 30, or 100 mg/kg/day by intragastric intubation between Gestation Days 20 and 50, targeting the period of organogenesis. At the maternal toxic doses of ≥ 30 mg/kg/day, increased abortion, vomiting, and diarrhea were observed. Smaller fetuses/reduced fetal body weights were observed at 100 mg/kg/day (2864 times the human AUC at the recommended human ophthalmic dose). The NOAEL for fetal toxicity was 10 mg/kg/day (174 times the human AUC at the recommended human ophthalmic dose).

In a pre- and postnatal study, rats were administered moxifloxacin by oral gavage at doses of 20, 100, and 500 mg/kg/day from Gestation Day 6 until the end of lactation. Maternal death occurred during gestation at 500 mg/kg/day. Slight increases in the duration of pregnancy, reduced pup birth weight, and decreased prenatal and neonatal survival were observed at 500 mg/kg/day (estimated 277 times the human AUC at the recommended human ophthalmic dose). The NOAEL for pre- and postnatal development was 100 mg/kg/day (estimated 30 times the human AUC at the recommended human ophthalmic dose).

8.2 Lactation

Risk Summary

There is no data regarding the presence of VIGAMOX®in human milk, the effects on the breastfed infants, or the effects on milk production/excretion to inform risk of VIGAMOX®to an infant during lactation.

A study in lactating rats has shown transfer of moxifloxacin into milk following oral administration.

Systemic levels of moxifloxacin following topical ocular administration are low [see Clinical Pharmacology (12.3)] , and it is not known whether measurable levels of moxifloxacin would be present in maternal milk following topical ocular administration.

The developmental and health benefits of breastfeeding should be considered along with the mother’s clinical need for VIGAMOX and any potential adverse effects on the breastfed child from VIGAMOX®.

8.4 Pediatric Use

The safety and effectiveness of VIGAMOX have been established in all ages. Use of VIGAMOX is supported by evidence from adequate and well controlled studies of VIGAMOX in adults, children, and neonates [see Clinical Studies (14)] .

There is no evidence that the ophthalmic administration of VIGAMOX has any effect on weight bearing joints, even though oral administration of some quinolones has been shown to cause arthropathy in immature animals.

8.5 Geriatric Use

No overall differences in safety and effectiveness have been observed between elderly and younger patients.

11 DESCRIPTION

VIGAMOX (moxifloxacin ophthalmic solution) 0.5% is a sterile solution for topical ophthalmic use. Moxifloxacin hydrochloride is an 8-methoxy fluoroquinolone anti-infective, with a diazabicyclononyl ring at the C7 position. The chemical name for moxifloxacin hydrochloride is 1-Cyclopropyl-6-fluoro-1,4-dihydro-8-methoxy-7-[(4aS,7aS)-octahydro-6H-pyrrolol[3,4b]pyridin-6-yl]-4-oxo-3-quinolinecarboxylic acid, monohydrochloride. The molecular formula for moxifloxacin hydrochloride is C21H24FN3O4•HCl and its molecular weight is 437.9 g/mol. The chemical structure is presented below:

Moxifloxacin hydrochloride is a slightly yellow to yellow crystalline powder.

Each mL of VIGAMOX solution contains 5.45 mg moxifloxacin hydrochloride, equivalent to 5 mg moxifloxacin base. VIGAMOX contains Active:Moxifloxacin 0.5% (5 mg/mL); Inactives:Boric acid, purified water, and sodium chloride. May also contain hydrochloric acid/sodium hydroxide to adjust pH to approximately 6.8.

VIGAMOX®is an isotonic solution with an osmolality of approximately 290 mOsm/kg.

12 CLINICAL PHARMACOLOGY

12.1 Mechanism of Action

Moxifloxacin is a member of the fluoroquinolone class of anti-infective drugs [see Microbiology (12.4)] .

12.3 Pharmacokinetics

Plasma concentrations of moxifloxacin were measured in healthy adult male and female subjects who received bilateral topical ocular doses of VIGAMOX®3 times a day. The mean steady-state Cmax(2.7 ng/mL) and AUC0-∞(41.9 ng●hr/mL) values were 1600 and 1100 times lower than the mean Cmaxand AUC reported after therapeutic 400 mg doses of moxifloxacin. The plasma half-life of moxifloxacin was estimated to be 13 hours.

12.4 Microbiology

The antibacterial action of moxifloxacin results from inhibition of the topoisomerase II (DNA gyrase) and topoisomerase IV. DNA gyrase is an essential enzyme that is involved in the replication, transcription and repair of bacterial DNA. Topoisomerase IV is an enzyme known to play a key role in the partitioning of the chromosomal DNA during bacterial cell division.

The mechanism of action for quinolones, including moxifloxacin, is different from that of macrolides, aminoglycosides, or tetracyclines. Therefore, moxifloxacin may be active against pathogens that are resistant to these antibiotics and these antibiotics may be active against pathogens that are resistant to moxifloxacin. There is no cross-resistance between moxifloxacin and the aforementioned classes of antibiotics. Cross-resistance has been observed between systemic moxifloxacin and some other quinolones.

In vitroresistance to moxifloxacin develops via multiple-step mutations. Resistance to moxifloxacin occurs in vitroat a general frequency of between 1.8 x 10^-9to less than 1 x 10^-11for gram-positive bacteria.

Moxifloxacin has been shown to be active against most strains of the following microorganisms, both in vitroand in clinical infections as described in the Indications and Usage section:

Aerobic Gram-Positive Microorganisms
Corynebacteriumspecies*
Micrococcus luteus*
Staphylococcus aureus
Staphylococcus epidermidis
Staphylococcus haemolyticus
Staphylococcus hominis
Staphylococcus warneri*
Streptococcus pneumoniae
Streptococcus viridansgroup

Aerobic Gram-Negative Microorganisms
Acinetobacter lwoffii*
Haemophilus influenza
Haemophilus parainfluenzae*

Other Microorganisms
Chlamydia trachomatis

*Efficacy for this organism was studied in fewer than 10 infections.

The following in vitrodata are also available, but their clinical significance in ophthalmic infections is unknown.The safety and effectiveness of VIGAMOX in treating ophthalmological infections due to these microorganisms have not been established in adequate and well-controlled trials.

The following organisms are considered susceptible when evaluated using systemic breakpoints. However, a correlation between the in vitrosystemic breakpoint and ophthalmological efficacy has not been established. The list of organisms is provided as guidance only in assessing the potential treatment of conjunctival infections. Moxifloxacin exhibits in vitrominimal inhibitory concentrations (MICs) of 2 microgram/mL or less (systemic susceptible breakpoint) against most (greater than or equal to 90%) strains of the following ocular pathogens.

Aerobic Gram-Positive Microorganisms
Listeria monocytogenes
Staphylococcus saprophyticus
Streptococcus agalactiae
Streptococcus mitis
Streptococcus pyogenes
StreptococcusGroup C, G, and F

Aerobic Gram-Negative Microorganisms
Acinetobacter baumannii
Acinetobacter calcoaceticus
Citrobacter freundii
Citrobacter koseri
Enterobacter aerogenes
Enterobacter cloacae
Escherichia coli
Klebsiella oxytoca
Klebsiella pneumoniae
Moraxella catarrhalis
Morganella morganii
Neisseria gonorrhoeae
Proteus mirabilis
Proteus vulgaris
Pseudomonas stutzeri

Anaerobic Microorganisms
Clostridium perfringens
Fusobacteriumspecies
Prevotellaspecies
Propionibacterium acnes

Other Microorganisms
Chlamydia pneumoniae
Legionella pneumophila
Mycobacterium avium
Mycobacterium marinum
Mycoplasma pneumoniae

13 NONCLINICAL TOXICOLOGY

13.1 Carcinogenesis, Mutagenesis, Impairment of Fertility

Carcinogenesis

Long-term studies in animals to determine the carcinogenic potential of moxifloxacin have not been performed. However, in an accelerated study with initiators and promoters, moxifloxacin was not carcinogenic in rats following up to 38 weeks of oral dosing at 500 mg/kg/day (3224 times the highest recommended total daily human ophthalmic dose for a 60 kg person, based on body surface area).

Mutagenesis

Moxifloxacin was not mutagenic in four bacterial strains used in the Ames Salmonellareversion assay. As with other quinolones, the positive response observed with moxifloxacin in strain TA 102 using the same assay may be due to the inhibition of DNA gyrase. Moxifloxacin was not mutagenic in the CHO/HGPRT mammalian cell gene mutation assay. An equivocal result was obtained in the same assay when V79 cells were used. Moxifloxacin was clastogenic in the V79 chromosome aberration assay, but it did not induce unscheduled DNA synthesis in cultured rat hepatocytes. There was no evidence of genotoxicity in vivoin a micronucleus test or a dominant lethal test in mice.

Impairment of Fertility

Moxifloxacin had no effect on fertility in male and female rats at oral doses as high as 500 mg/kg/day, approximately 3224 times the highest recommended total daily human ophthalmic dose, based on body surface area. At 500 mg/kg/day orally, there were slight effects on sperm morphology (head-tail separation) in male rats and on the estrous cycle in female rats.

14 CLINICAL STUDIES

In two randomized, double-masked, multicenter, controlled clinical trials in which patients were dosed 3 times a day for 4 days, VIGAMOX®produced clinical cures on Day 5-6 in 66% to 69% of patients treated for bacterial conjunctivitis. Microbiological success rates for the eradication of baseline pathogens ranged from 84% to 94%.

In a randomized, double-masked, multicenter, parallel-group clinical trial of pediatric patients with bacterial conjunctivitis between birth and 31 days of age, patients were dosed with VIGAMOX or another anti-infective agent. Clinical outcomes for the trial demonstrated a clinical cure rate of 80% at Day 9 and a microbiological eradication success rate of 92% at Day 9.

Please note that microbiologic eradication does not always correlate with clinical outcome in anti-infective trials.

16 HOW SUPPLIED/STORAGE AND HANDLING

VIGAMOX®is supplied as a sterile ophthalmic solution in a dispensing system consisting of a natural low density polyethylene bottle and dispensing plug and tan polypropylene closure.

3 mL in a 4 mL bottle NDC 82667-700-03

Storage: Store at 2°C to 25°C (36°F to 77°F).

17 PATIENT COUNSELING INFORMATION

Avoid Contamination of the Product

Advise patients not to touch the dropper tip to any surface to avoid contaminating the contents.

Avoid Contact Lens Wear

Advise patients not to wear contact lenses if they have signs and symptoms of bacterial conjunctivitis [see Warnings and Precautions (5.3)] .

Hypersensitivity Reactions

Systemically administered quinolones including moxifloxacin have been associated with hypersensitivity reactions, even following a single dose. Instruct patients to discontinue use immediately and contact their physician at the first sign of a rash or allergic reaction [see Warnings and Precautions (5.1)] .

Distributed by:

Harrow Eye, LLC™

Nashville, TN, USA

HARROW®

PRINCIPAL DISPLAY PANEL

NDC 82667-700-03

STERILE

VIGAMOX®

(moxifloxacin ophthalmic solution)
0.5%

3 mL

HARROW®